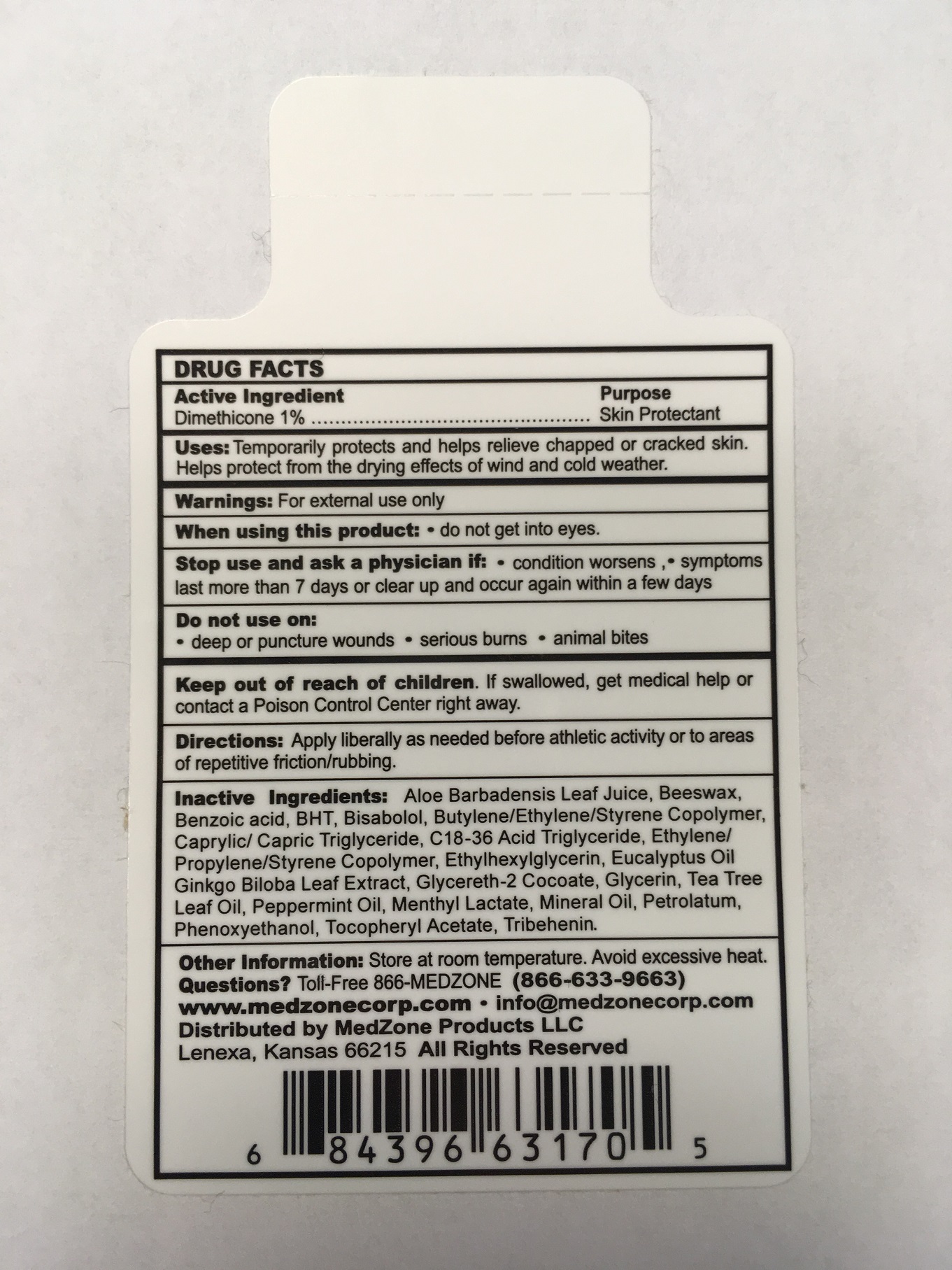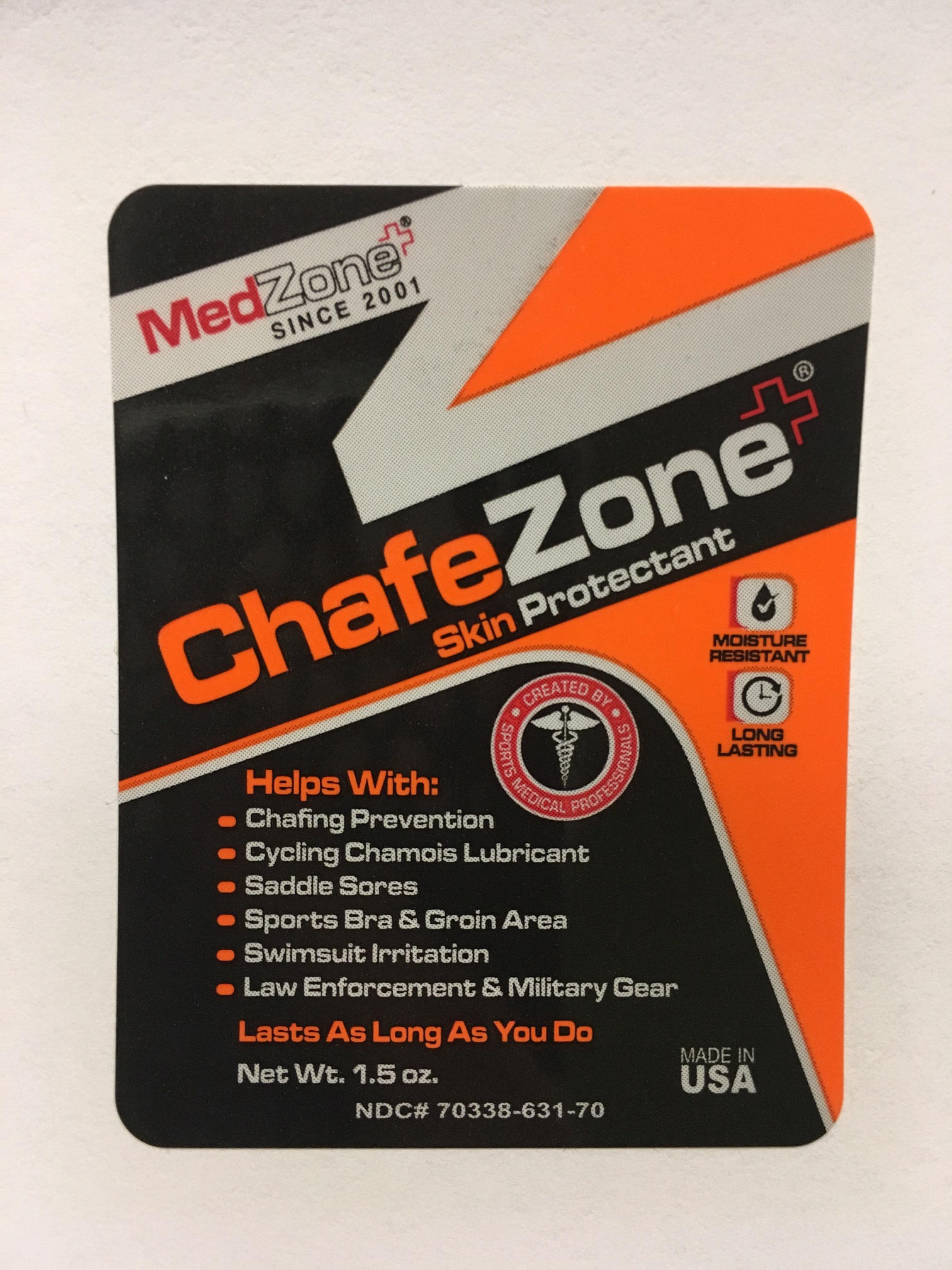 DRUG LABEL: ChafeZone
NDC: 70338-631 | Form: STICK
Manufacturer: Medzone Products LLC
Category: otc | Type: HUMAN OTC DRUG LABEL
Date: 20211231

ACTIVE INGREDIENTS: DIMETHICONE 10 mg/1 g
INACTIVE INGREDIENTS: BENZOIC ACID; ETHYLHEXYLGLYCERIN; ALOE VERA LEAF; ALPHA-TOCOPHEROL ACETATE; C18-36 ACID TRIGLYCERIDE; EUCALYPTUS OIL; GINKGO; LEVOMENOL; MEDIUM-CHAIN TRIGLYCERIDES; MENTHYL LACTATE, (-)-; MINERAL OIL; PETROLATUM; PROPYLENE; STYRENE; TRIBEHENIN; YELLOW WAX; TEA TREE OIL; PEPPERMINT OIL; PHENOXYETHANOL; GLYCERETH-2 COCOATE; 1-BUTENE

ChafeZone

DRUG FACTS Active Ingredient

Active Ingredient | Purpose
Dimethicone 1% | Skin Protectant

Purpose

Skin Protectant

Uses:

Temporarily protects and helps relieve chapped or cracked skin. Helps protect from the drying effects of wind and cold weather.

Warnings

For external use only.

When using this product:

- do not get into eyes

Stop use and ask a physician if:

- condition worsens
- symptoms last more than 7 days or clear up and occur again within a few days

Do not use on:

- deep or puncture wounds
- serious burns
- animal bites

Keep out of reach of children.

If swallowed, get medical help or contact a Poison Control Center right away.

Directions:

Apply liberally as needed before athletic activity or to areas of repetitive friction/rubbing.

Inactive Ingredients:

Aloe Barbadensis Leaf Juice, Beeswax, Benzoic Acid, BHT, Bisabolol, Butylene/ethylene/styrene Copolymer, Caprylic Capric Triglyceride, C18-36 Acid Triglyceride, ethylene/propylene/styrene copolymer, ethylhexylglycerin, eucalyptus oil, ginkgo biloba leaf extract, glycereth-2 cocoate, glycerin, tea tree leaf oil, peppermint oil, Menthyl lactate, mineral oil, petrolatum, phenoxyethanol, tocopheryl acetate, tribehenin.

Other Information:

Store at room temperature. Avoid excessive heat.

Questions?

Toll-Free 866-MEDZONE (866-633-9663)

www.medzonecorp.com info@medzonecorp.com

Distributed by

MedZone Products, LLC

Lenexa, Kansas 66215

All Rights Reserved